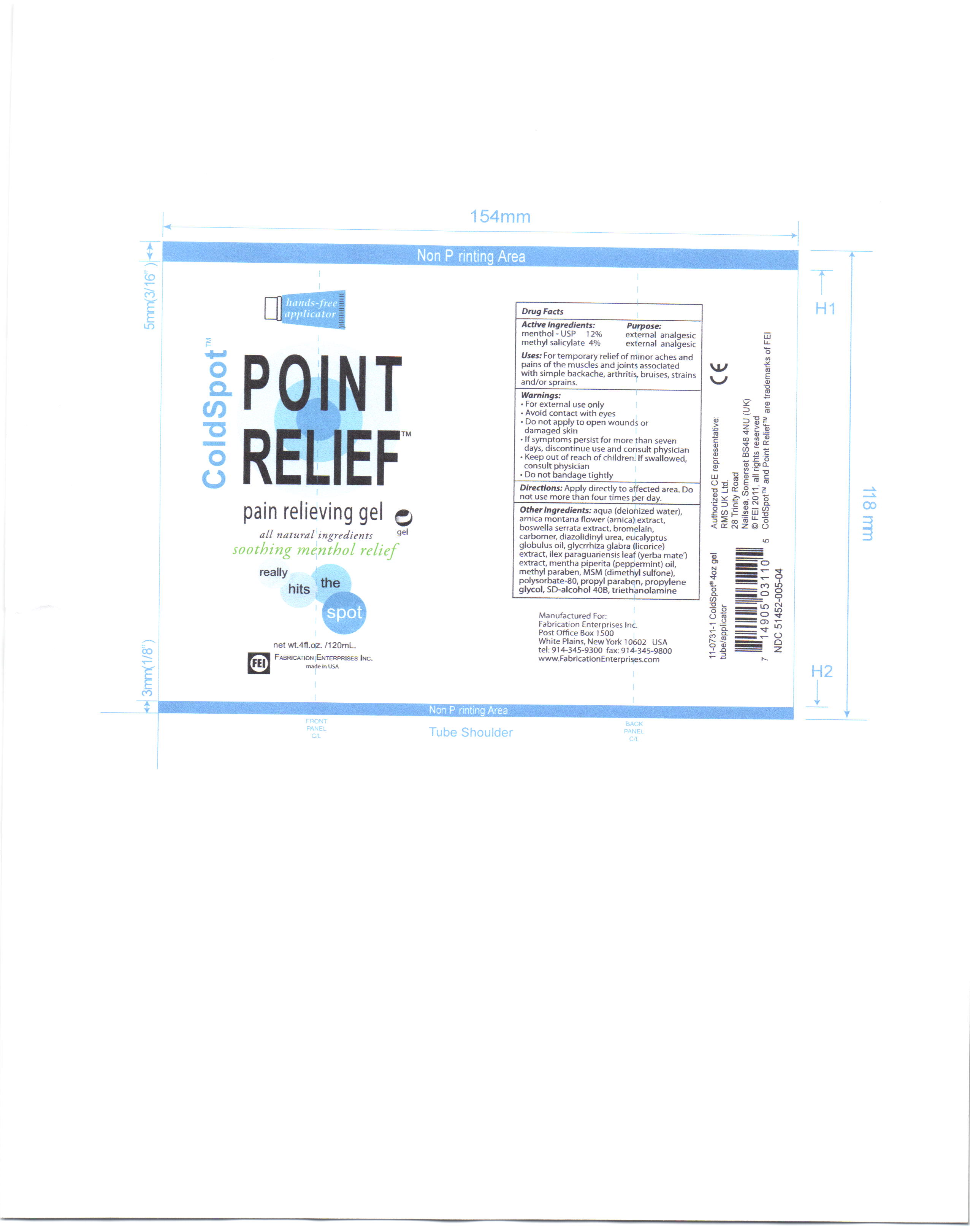 DRUG LABEL: Cold Spot
NDC: 51452-005 | Form: GEL
Manufacturer: Fabrication Enterprises, inc. 
Category: otc | Type: HUMAN OTC DRUG LABEL
Date: 20111013

ACTIVE INGREDIENTS: MENTHOL 14.4 mL/120 mL; METHYL SALICYLATE 4.8 mL/120 mL
INACTIVE INGREDIENTS: WATER; ARNICA MONTANA FLOWER; BOSWELLIA SERRATA RESIN OIL; BROMELAINS; CARBOMER 1342; Eucalyptus Globulus leaf; ILEX PARAGUARIENSIS LEAF; Peppermint Oil; Dimethyl Sulfone; GLYCYRRHIZA GLABRA; alcohol; DIAZOLIDINYL UREA; METHYLPARABEN; POLYSORBATE 80; PROPYLENE GLYCOL; PROPYLPARABEN

coldspot point relief

ACTIVE INGREDIENT

menthol - usp 12%

methyl salicylate 4%

INACTIVE INGREDIENT

aqua (deionized water), arnica montana flower (arnica) extract, boswella serrata extract, brtomelain, carbomer, diazolidinyl urea, eucalyptus globulus oil, glycrrhiza glabra (licorice) extract, ilex paraguariensis leaf (yerba mate) extract, menth piperita (pepperment) oil, methyl paraben, MSM (dimethyl sulfone) polysorbate-80, SD-alcohol 40B, triethanolamine

Keep out of reach of children. If swallowed, consult physician.

WARNINGS

for external use only

avoid contact with eyes

do not apply to open wounds or damaged skin

if symptoms persist for more than seven days, discontinue use and consult physician

keep out of reach of children. if swallowed, consult physician

do not bandage tightly

INDICATIONS AND USAGE

for temporary relief of minor aches and pains of the muscles and joints associated with simple backache, arthritis, bruises, strains and/or sprains.

DOSAGE AND ADMINISTRATION

apply directly to affected area. do not use more than four times per day.

PURPOSE

for temporary relief of minor aches and pains of the muscles and joints associated with simple backache, arthritis, bruises, strains and/or sprians.